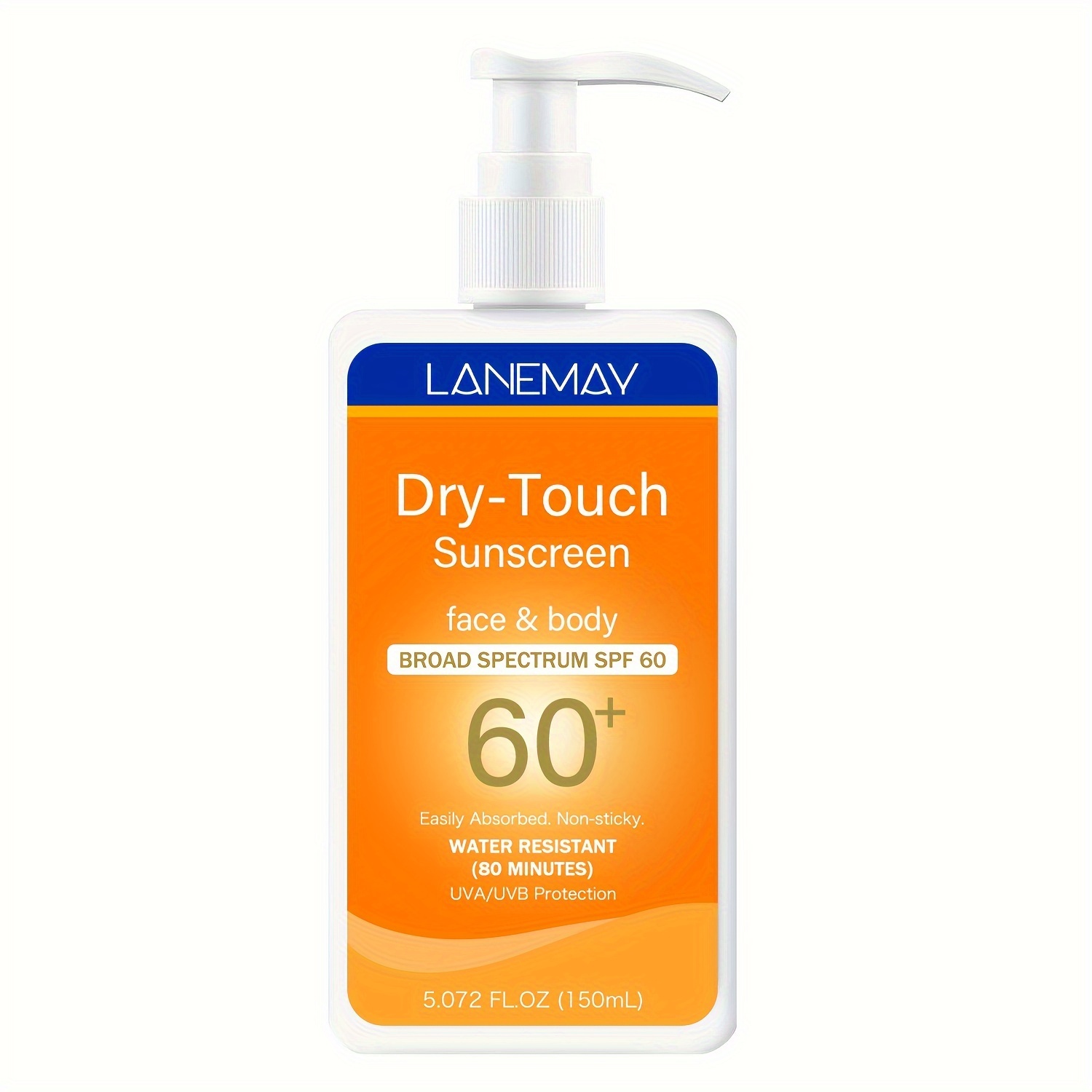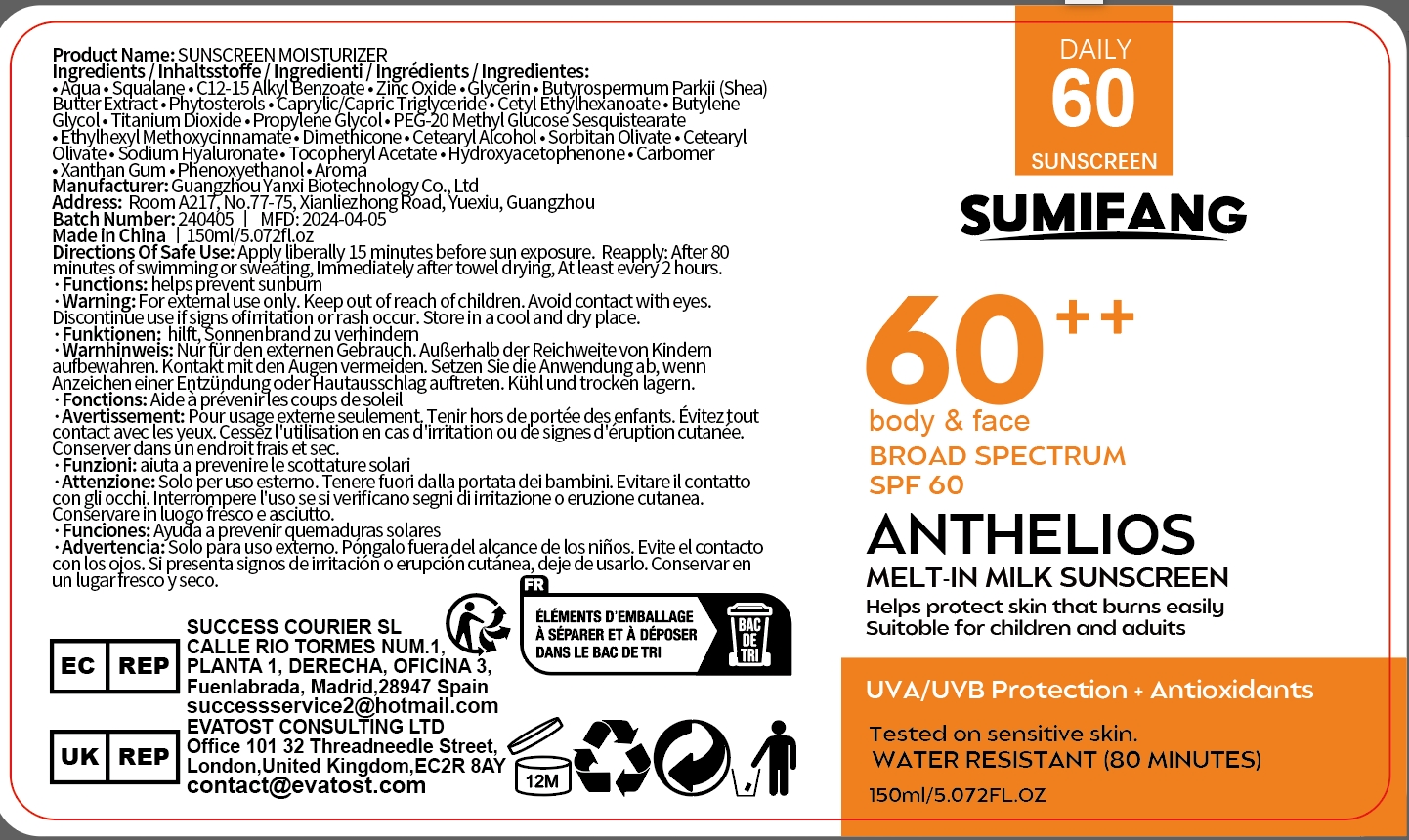 DRUG LABEL: SUNSCREEN MOISTURIZER
NDC: 84025-038 | Form: CREAM
Manufacturer: Guangzhou Yanxi Biotechnology Co., Ltd
Category: otc | Type: HUMAN OTC DRUG LABEL
Date: 20240524

ACTIVE INGREDIENTS: ZINC OXIDE 3 mg/100 mL; SQUALANE 5 mg/100 mL
INACTIVE INGREDIENTS: WATER

DOSAGE AND ADMINISTRATION

use as a normal sunscreen

WARNINGS

For external use only.

INACTIVE INGREDIENT

AQUA

PURPOSE

helps prevent sunburn

Keep out of reach of children.

INDICATIONS AND USAGE

Apply liberally 15 minutes before sun exposure. Reapply: After 80 minutes of swimming or sweating, Immediately after towel drying, At least every 2 hours.